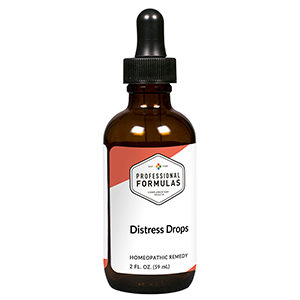 DRUG LABEL: Distress Drops
NDC: 63083-2121 | Form: LIQUID
Manufacturer: Professional Complementary Health Formulas
Category: homeopathic | Type: HUMAN OTC DRUG LABEL
Date: 20190815

ACTIVE INGREDIENTS: AVENA SATIVA FLOWERING TOP 1 [hp_X]/59 mL; FERULA ASSA-FOETIDA RESIN 3 [hp_X]/59 mL; DICENTRA CANADENSIS ROOT 3 [hp_X]/59 mL; HYOSCYAMUS NIGER 3 [hp_X]/59 mL; FERULA SUMBUL ROOT 6 [hp_X]/59 mL; VALERIAN 3 [hp_X]/59 mL; CICUTA VIROSA WHOLE 4 [hp_X]/59 mL; STRYCHNOS IGNATII SEED 4 [hp_X]/59 mL; GAULTHERIA PROCUMBENS TOP 4 [hp_X]/59 mL; DELPHINIUM STAPHISAGRIA SEED 4 [hp_X]/59 mL
INACTIVE INGREDIENTS: ALCOHOL; WATER

C121

ACTIVE INGREDIENTS

Avena sativa 1X
Asafoetida 3X
Corydalis canadensis 3X
Hyoscyamus niger 3X
Sumbul 6X
Valeriana officinalis 3X
Cicuta virosa 4X
Ignatia amara 4X
Olei gaultheria procumbens 4X
Staphysagria 4X

QUESTIONS

Professional Formulas

PO Box 2034 Lake Oswego, OR 97035

INDICATIONS

For the temporary relief of feeling distressed or a tendency towards overreaction.*

PURPOSE

*Claims based on traditional homeopathic practice, not accepted medical evidence. Not FDA evaluated.

WARNINGS

In case of overdose, get medical help or contact a poison control center right away.

Keep out of the reach of children.

PREGNANCY OR BREAST FEEDING

If pregnant or breastfeeding, ask a healthcare professional before use.

DIRECTIONS

Place drops under tongue 30 minutes before/after meals. Adults and children 12 years and over: Take 10 drops up to 3 times per day. Consult a physician for use in children under 12 years of age.

OTHER INFORMATION

Tamper resistant. If seal is broken, do not use. After opening, close container tightly and store at room temperature away from heat.

INACTIVE INGREDIENTS

20% ethanol, purified water.

LABEL

Est 1985

Professional Formulas

Complementary Health

Distress Drops

Homeopathic Remedy

2 FL. OZ. (59 mL)